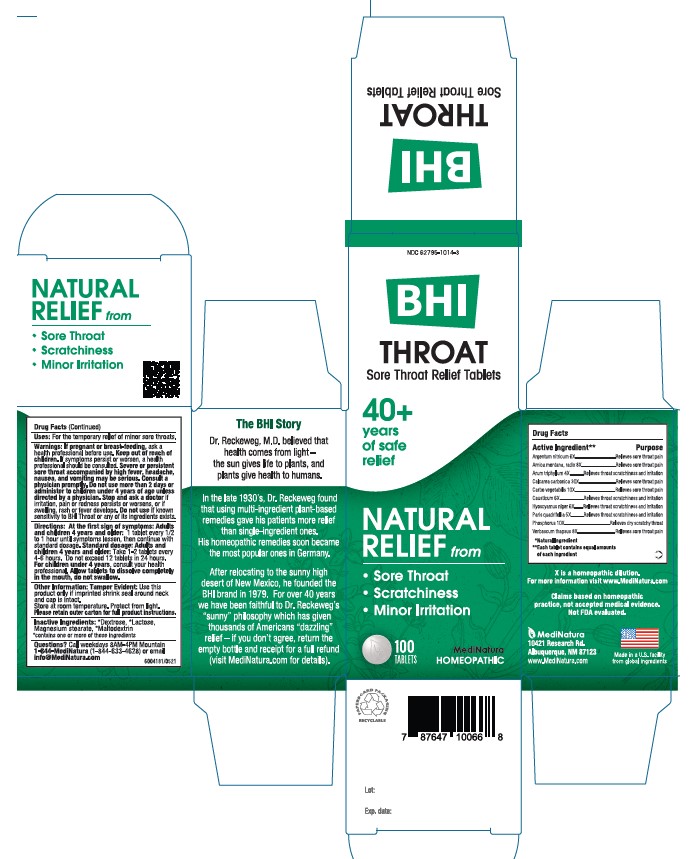 DRUG LABEL: BHI Throat
NDC: 62795-1014 | Form: TABLET
Manufacturer: MediNatura Inc
Category: homeopathic | Type: HUMAN OTC DRUG LABEL
Date: 20220711

ACTIVE INGREDIENTS: SILVER NITRATE 6 [hp_X]/1 1; ARNICA MONTANA ROOT 8 [hp_X]/1 1; ARISAEMA TRIPHYLLUM ROOT 4 [hp_X]/1 1; OYSTER SHELL CALCIUM CARBONATE, CRUDE 30 [hp_X]/1 1; ACTIVATED CHARCOAL 10 [hp_X]/1 1; CAUSTICUM 6 [hp_X]/1 1; HYOSCYAMUS NIGER 6 [hp_X]/1 1; PARIS QUADRIFOLIA 5 [hp_X]/1 1; PHOSPHORUS 10 [hp_X]/1 1; VERBASCUM THAPSUS 8 [hp_X]/1 1
INACTIVE INGREDIENTS: LACTOSE; MAGNESIUM STEARATE; MALTODEXTRIN; DEXTROSE

BHI Throat Tablet

ACTIVE INGREDIENTS

Each tablet contains: Argentum nitricum 6X, *Arnica montana, radix 8X, *Arum triphyllum 4X, Calcarea carbonica 30X, *Carbo vegetabilis 10X, Causticum 6X, *Hyoscyamus niger 6X, *Paris quadrifolia 5X, *Phosphorus 10X, *Verbascum thapsus 8X 30 mg each.

*Natural Ingredients

INACTIVE INGREDIENT

Inactive Ingredients: **Dextrose, ** Lactose, Magnesium Stearate, **Maltodextrin
**contains one or more of these ingredients.

PURPOSE

Sore Throat Relief Tablets

Relieves:

• Sore Throat

• Scratchiness

• Minor Irritation

USES

For the temporary relief of minor sore throat, throat scratchiness, throat irritation

DIRECTIONS

At first sign of symptoms: Adults and children 4 years and older: 1 tablet every 1/2 to 1 hour until symptoms lessen, then continue with standard dosage.

Standard dosage: Adults and children 4 years and older: Take 1-2 tablets every 4 to 6 hours. Do not exceed 12 tablets in 24 hours.

For children under 4, consult your health professional.

Allow tablets to dissolve completely in the mouth, do not swallow

.

WARNINGS

If pregnant or breast-feeding , ask a health professional before use. Keep out of reach of children. If symptoms persist or worsen, a health professional should be consulted. Severe or persistent sore throat accompanied by high fever, headache, nausea, and vomiting may be serious. Consult physician promptly. Do not use more than 2 days or administer to children under 4 years of age unless directed by a physician. Stop and ask a doctor if irritation, pain or redness persists or worsens, or if swelling, rash or fever develops.Do not use if known sensitivity to Throat or any of its ingredients exists.

KEEP OUT OF REACH OF CHILDREN